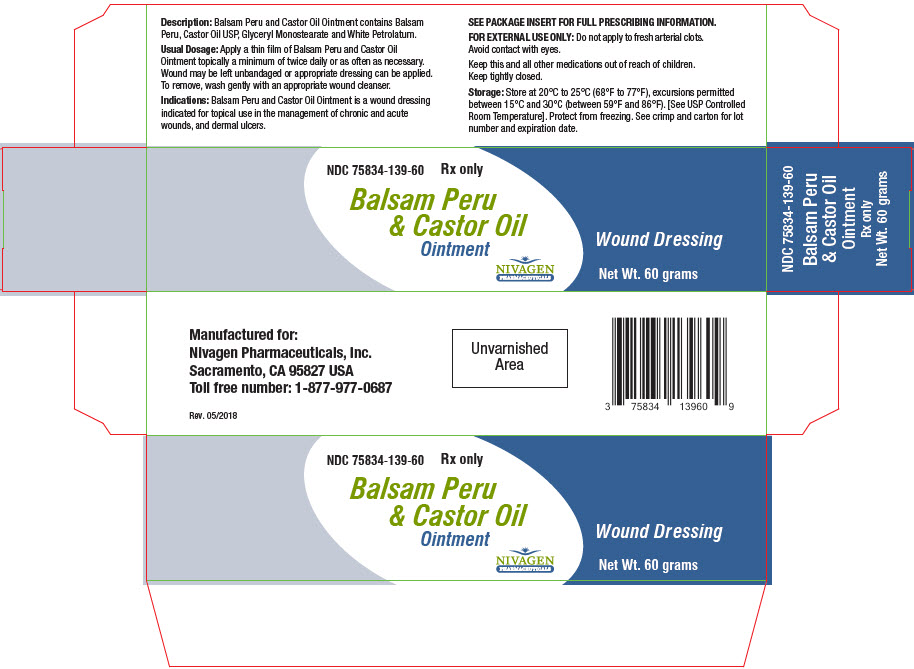 DRUG LABEL: BALSAM PERU AND CASTOR OIL
NDC: 75834-139 | Form: OINTMENT
Manufacturer: Nivagen Pharmaceuticals, Inc.
Category: other | Type: MEDICAL DEVICE
Date: 20260114

Balsam Peru & Castor Oil Ointment

NDC 75834-139-60

Rx Only

Wound Dressing

DESCRIPTION

Balsam Peru & Castor Oil Ointment contains Balsam Peru, Castor Oil USP, Glyceryl Monostearate and White Petrolatum.

ACTION

Balsam Peru & Castor Oil Ointment helps to deodorize and protectively cover pressure wounds (ulcers) and may help with the reduction of pain. Balsam Peru & Castor Oil Ointment provides a moist wound environment conductive to healing. The moisturizing properties of Balsam Peru & Castor Oil Ointment also help in the prevention of cracking around the edges of sores.

INDICATIONS

Balsam Peru & Castor Oil Ointment is a wound dressing for topical use in the management of chronic and acute wounds, and dermal ulcers including: pressure ulcers (Stage I-IV), venous stasis ulcers, diabetic ulcers, first and second degree burns, surgical wounds, traumatic wounds, superficial wounds, ulcers resulting from arterial insufficiency and grafted wound/donor sites.

CONTRAINDICATIONS

Balsam Peru & Castor Oil Ointment is contraindicated in persons who have shown hypersensitivity to Balsam Peru, Petrolatum or any of the other ingredients used in this ointment.

USES

Balsam Peru & Castor Oil Ointment is easy to apply and quickly reduces odors frequently accompanying a decubitus ulcer. The wound may be left open or appropriate dressing applied. Please note that wounds generally heal poorly in the presence of hemoglobin or zinc deficiency.

WARNING

FOR EXTERNAL USE ONLY. Do not apply to fresh arterial clots. Avoid contact with eyes. Keep this and all other medications out of reach of children. Keep tightly closed. Use only as directed by a physician. When applied to a sensitive area, a temporary stinging may occur.

USUAL DOSAGE

Apply a thin film of Balsam Peru & Castor Oil Ointment topically a minimum of twice daily or as often as necessary. Wound may be left unbandaged or appropriate dressing can be applied. To remove, wash gently with an appropriate wound cleanser.

HOW SUPPLIED

Balsam Peru & Castor Oil Ointment is supplied as follows:

SIZE | NDC NUMBER
60 GRAM TUBE | 75834-139-60

STORAGE

Store at 20°C to 25°C (68°F to 77°F), excursions permitted between 15°C and 30°C (between 59°F and 86°F). Brief exposure to temperatures up to 40°C (104°F) may be tolerated provided the mean kinetic temperature does not exceed 25°C (77°F); however, such exposure should be minimized. [See USP Controlled Room Temperature]. Protect from freezing. See crimp for lot number and expiration date.

Manufactured for:
Nivagen Pharmaceuticals, Inc.
Sacramento, CA 95827 USA
Toll free number: 1-877-977-0687

Rev. 07/18

PRINCIPAL DISPLAY PANEL - 60 gram Tube Carton

NDC 75834-139-60
Rx only

Balsam Peru
& Castor Oil
Ointment

NIVAGEN
PHARMACEUTICALS

Wound Dressing

Net Wt. 60 grams